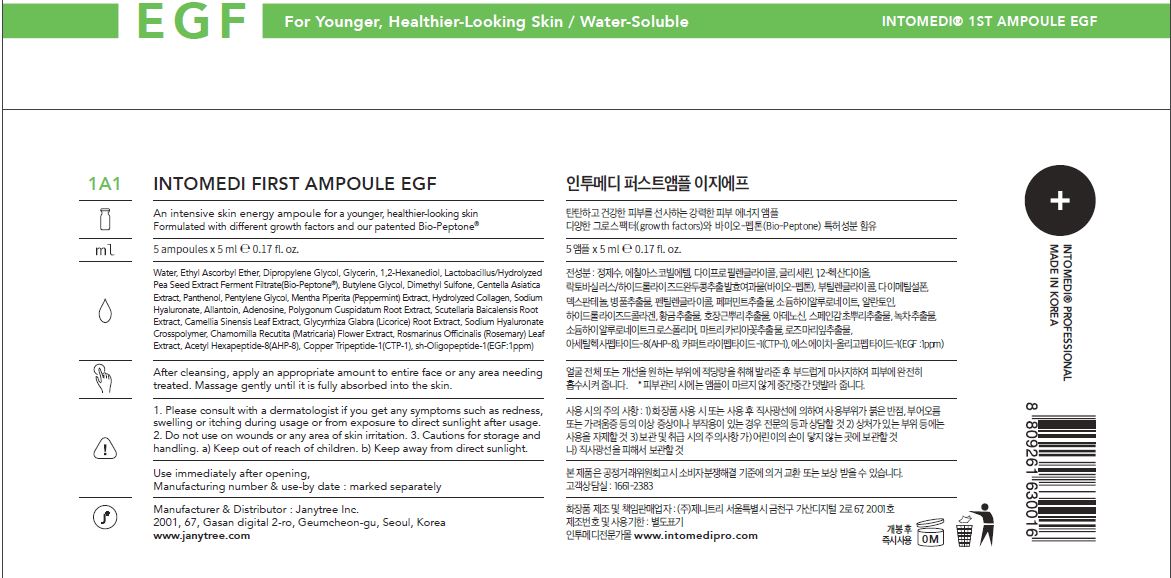 DRUG LABEL: INTOMEDI FIRST AMPOULE EGF
NDC: 82879-0003 | Form: LIQUID
Manufacturer: Janytree Inc.
Category: otc | Type: HUMAN OTC DRUG LABEL
Date: 20220712

ACTIVE INGREDIENTS: ADENOSINE 0.04 g/100 mL
INACTIVE INGREDIENTS: BUTYLENE GLYCOL; WATER; GLYCERIN

INACTIVE INGREDIENTS

Water, Ethyl Ascorbyl Ether, Dipropylene Glycol, Glycerin, 1,2-Hexanediol, Lactobacillus/Hydrolyzed
Pea Seed Extract Ferment Filtrate(Bio-Peptone®), Butylene Glycol, Dimethyl Sulfone, Centella Asiatica
Extract, Panthenol, Pentylene Glycol, Mentha Piperita (Peppermint) Extract, Hydrolyzed Collagen, Sodium
Hyaluronate, Allantoin, Polygonum Cuspidatum Root Extract, Scutellaria Baicalensis Root
Extract, Camellia Sinensis Leaf Extract, Glycyrrhiza Glabra (Licorice) Root Extract, Sodium Hyaluronate
Crosspolymer, Chamomilla Recutita (Matricaria) Flower Extract, Rosmarinus Officinalis (Rosemary) Leaf
Extract, Acetyl Hexapeptide-8(AHP-8), Copper Tripeptide-1(CTP-1), sh-Oligopeptide-1(EGF:1ppm)

ACTIVE INGREDIENTS

adenosine

PURPOSE

An intensive skin energy ampoule for a younger, healthier-looking skin
Formulated with different growth factors and our patented Bio-Peptone®

WARNINGS

For external use only When using this product
■ If following abnormal symptoms occurs after using the product, stop using the product and consult with a skin specialist. Symptoms : Red specks, swelling, itching
■ Do not use on the skin parts affected by wound, eczema, or dermatitis.
Keep out of reach of children.
■ If swallowed, get a medical help or contact a person in control center immediately.
■ Avoid contact with eyes.

KEEP OUT OF REACH OF CHILDREN

If swallowed, get a medical help or contact a person in control center immediately.

INDICATIONS AND USAGE

apply a proper amount to the skin, and massage gently until fully absorbed

DOSAGE AND ADMINISTRATION

for external use only